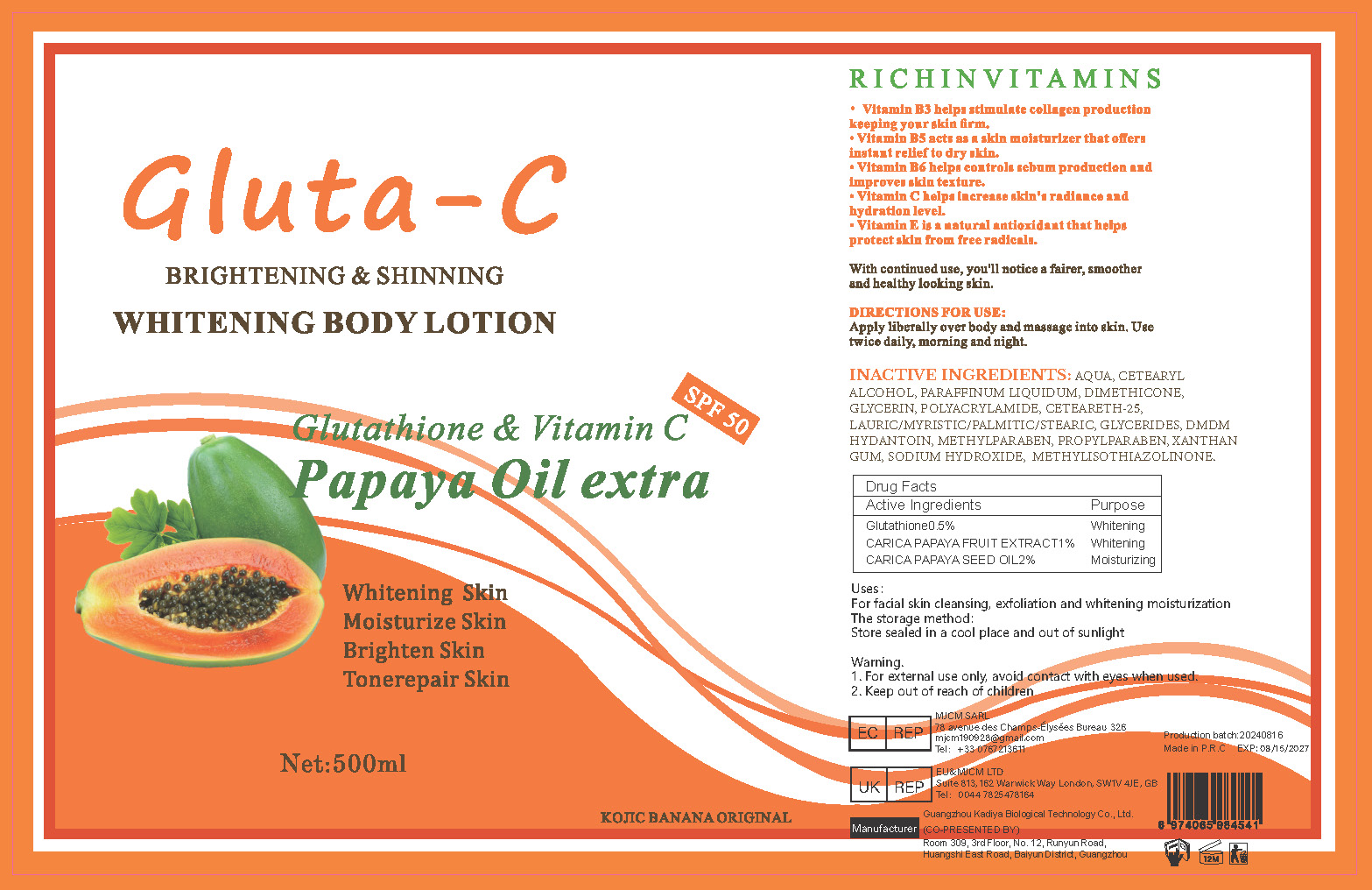 DRUG LABEL: Papaya Oil Whitening BodyLotion
NDC: 84423-041 | Form: EMULSION
Manufacturer: Guangzhou Kadiya Biotechnology Co., Ltd.
Category: otc | Type: HUMAN OTC DRUG LABEL
Date: 20240827

ACTIVE INGREDIENTS: GLUTATHIONE 2.5 mg/500 mL; PAPAYA SEED OIL 10 mg/500 mL; CARICA PAPAYA WHOLE 5 mg/500 mL
INACTIVE INGREDIENTS: METHYLISOTHIAZOLINONE; CETOSTEARYL ALCOHOL; POLYACRYLAMIDE (10000 MW); DMDM HYDANTOIN; SODIUM HYDROXIDE; GLYCERIN; CETEARETH-25; METHYLPARABEN; XANTHAN GUM; PROPYLPARABEN; DIMETHICONE; WATER; MINERAL OIL

PURPOSE

For facial skin cleansing, exfoliation and whitening moisturization

INACTIVE INGREDIENT

AQUA、CETEARYL ALCOHOL、PARAFFINUM LIQUIDUM、DIMETHICONE、GLYCERIN、POLYACRYLAMIDE、CETEARETH-25、LAURIC/MYRISTIC/PALMITIC/STEARIC、GLYCERIDES、DMDM HYDANTOIN、METHYLPARABEN、PROPYLPARABEN、XANTHAN GUM、SODIUM HYDROXIDE、 METHYLISOTHIAZOLINONE

WARNINGS

1、For external use only, avoid contact with eyes when used
2、Keep out of reach of children

INDICATIONS AND USAGE

With continued use, you'll notice a fairer, smoother and healthy looking skin.

DOSAGE AND ADMINISTRATION

Apply liberally over body and massage into skin. Use twice daily, morning and night.

KEEP OUT OF REACH OF CHILDREN SECTION

Active Ingredients
Glutathione0.5%
CARICA PAPAYA FRUIT EXTRACT1%
CARICA PAPAYA SEED OIL2%

PACKAGE LABEL

Active Ingredients
Glutathione0.5%
CARICA PAPAYA FRUIT EXTRACT1%
CARICA PAPAYA SEED OIL2%

Uses：
For facial skin cleansing, exfoliation and whitening moisturization
The storage method：
Store sealed in a cool place and out of sunlight

Warning.
1、For external use only, avoid contact with eyes when used
2、Keep out of reach of children

Inactive ingredients：
AQUA、CETEARYL ALCOHOL、PARAFFINUM LIQUIDUM、DIMETHICONE、GLYCERIN、POLYACRYLAMIDE、CETEARETH-25、LAURIC/MYRISTIC/PALMITIC/STEARIC、GLYCERIDES、DMDM HYDANTOIN、METHYLPARABEN、PROPYLPARABEN、XANTHAN GUM、SODIUM HYDROXIDE、 METHYLISOTHIAZOLINONE